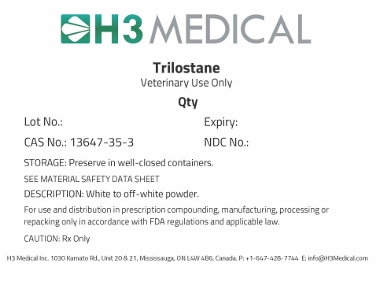 DRUG LABEL: Trilostane
NDC: 63732-2018 | Form: POWDER
Manufacturer: H3 Medical Inc
Category: other | Type: BULK INGREDIENT - ANIMAL DRUG
Date: 20171204

ACTIVE INGREDIENTS: TRILOSTANE 1 g/1 g

Trilostane